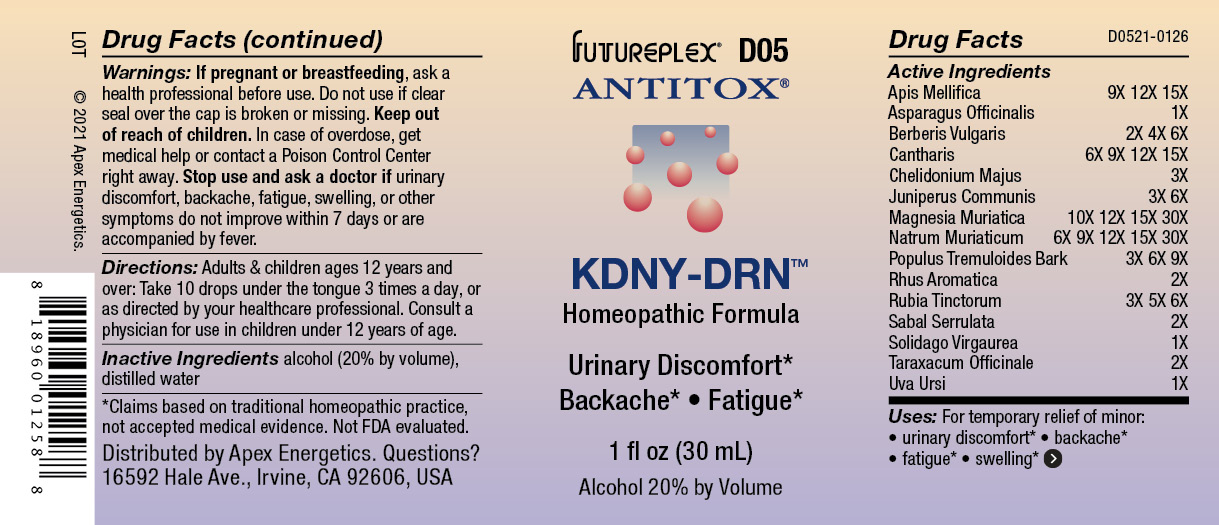 DRUG LABEL: D05
NDC: 63479-0405 | Form: SOLUTION
Manufacturer: Apex Energetics Inc.
Category: homeopathic | Type: HUMAN OTC DRUG LABEL
Date: 20240108

ACTIVE INGREDIENTS: APIS MELLIFERA 15 [hp_X]/1 mL; ASPARAGUS 1 [hp_X]/1 mL; BERBERIS VULGARIS ROOT BARK 6 [hp_X]/1 mL; LYTTA VESICATORIA 15 [hp_X]/1 mL; CHELIDONIUM MAJUS 3 [hp_X]/1 mL; JUNIPER BERRY 6 [hp_X]/1 mL; MAGNESIUM CHLORIDE 30 [hp_X]/1 mL; SODIUM CHLORIDE 30 [hp_X]/1 mL; POPULUS TREMULOIDES BARK 9 [hp_X]/1 mL; RHUS AROMATICA ROOT BARK 2 [hp_X]/1 mL; RUBIA TINCTORUM ROOT 6 [hp_X]/1 mL; SAW PALMETTO 2 [hp_X]/1 mL; SOLIDAGO VIRGAUREA FLOWERING TOP 1 [hp_X]/1 mL; TARAXACUM OFFICINALE 2 [hp_X]/1 mL; ARCTOSTAPHYLOS UVA-URSI LEAF 1 [hp_X]/1 mL
INACTIVE INGREDIENTS: ALCOHOL; WATER

D05

Active Ingredients
Apis Mellifica | 9X 12X 15X
Asparagus Officinalis | 1X
Berberis Vulgaris | 2X 4X 6X
Cantharis | 6X 9X 12X 15X
Chelidonium Majus | 3X
Juniperus Communis | 3X 6X
Magnesia Muriatica | 10X 12X 15X 30X
Natrum Muriaticum | 6X 9X 12X 15X 30X
Populus Tremuloides Bark | 3X 6X 9X
Rhus Aromatica | 2X
Rubia Tinctorum | 3X 5X 6X
Sabal Serrulata | 2X
Solidago Virgaurea | 1X
Taraxacum Officinale | 2X
Uva Ursi | 1X

INDICATIONS AND USAGE

Uses:

For temporary relief of minor:

urinary discomfort*

backache*

fatigue*

swelling*

*Claims based on traditional homeopathic practice, not accepted medical evidence. Not FDA evaluated.

Warnings

PREGNANCY OR BREAST FEEDING

If pregnant or breastfeeding, ask a health professional before use.

Do not use if clear seal over the cap is broken or missing.

Keep out of reach of children. In case of overdose, get medical help or contact a Poison Control Center right away.

Stop use and ask a doctor if urinary discomfort, backache, fatigue, swelling, or other symptoms do not improve within 7 days or are accompanied by fever.

Directions:

Adults & children ages 12 years and over: Take 10 drops under the tongue 3 times a day, or as directed by your healthcare professional. Consult a physician for use in children under 12 years of age.

Inactive Ingredients

alcohol (20% by volume), distilled water

Distributed by Apex Energetics. Questions?
16592 Hale Ave., Irvine, CA 92606, USA

PACKAGE LABEL

FUTUREPLEX® D05

ANTITOX®

KDNY-DRN™

Homeopathic Formula

Urinary Discomfort

Backache • Fatigue

1 fl oz (30 mL)

Alcohol 20% by Volume